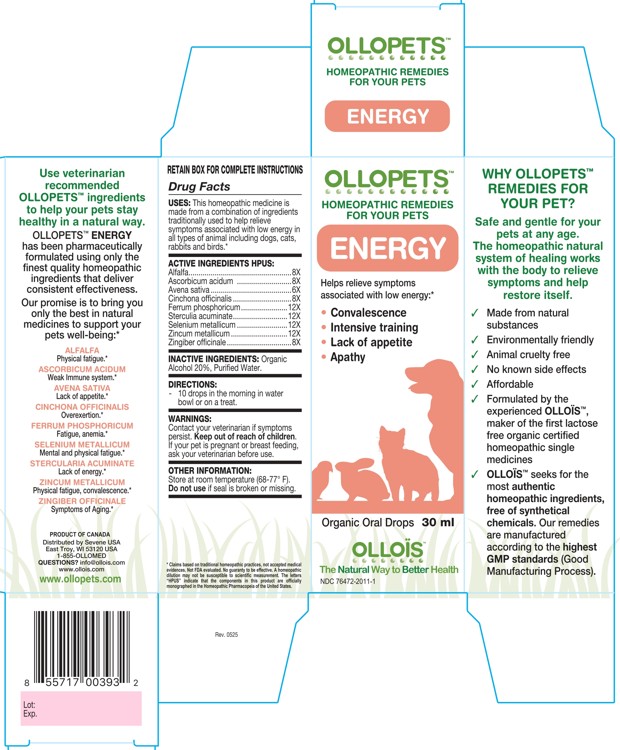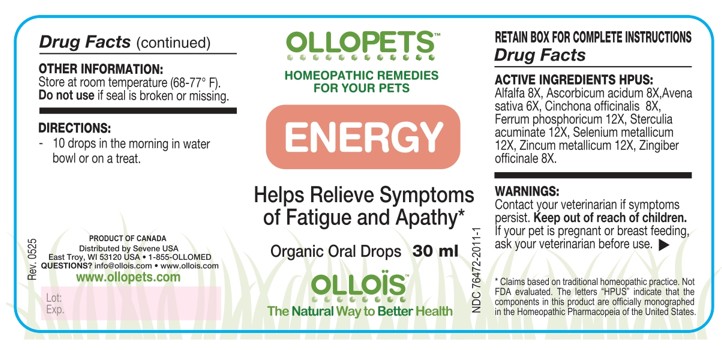 DRUG LABEL: OLLOPETS ENERGY
NDC: 76472-2011 | Form: SOLUTION
Manufacturer: SEVENE USA
Category: homeopathic | Type: OTC ANIMAL DRUG LABEL
Date: 20260218

ACTIVE INGREDIENTS: ALFALFA 8 [hp_X]/100 mL; ASCORBIC ACID 8 [hp_X]/100 mL; AVENA SATIVA TOP 6 [hp_X]/100 mL; CINCHONA OFFICINALIS BARK 8 [hp_X]/100 mL; FERROSOFERRIC PHOSPHATE 7 [hp_C]/100 mL; COLA ACUMINATA SEED 12 [hp_X]/100 mL; SELENIUM 12 [hp_X]/100 mL; ZINC 12 [hp_X]/100 mL; GINGER 8 [hp_X]/100 mL
INACTIVE INGREDIENTS: ALCOHOL; WATER

SEVENE USA - OLLOPETS - ENERGY

ACTIVE INGREDIENT HPUS

Alfalfa...................................................8X
Ascorbicum acidum ...........................8X
Avena sativa ........................................6X
Cinchona officinalis .............................8X
Ferrum phosphoricum.......................12X
Sterculia acuminate...........................12X
Selenium metallicum .........................12X
Zincum metallicum ............................12X
Zingiber officinale ................................8X